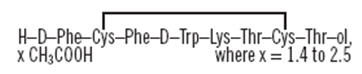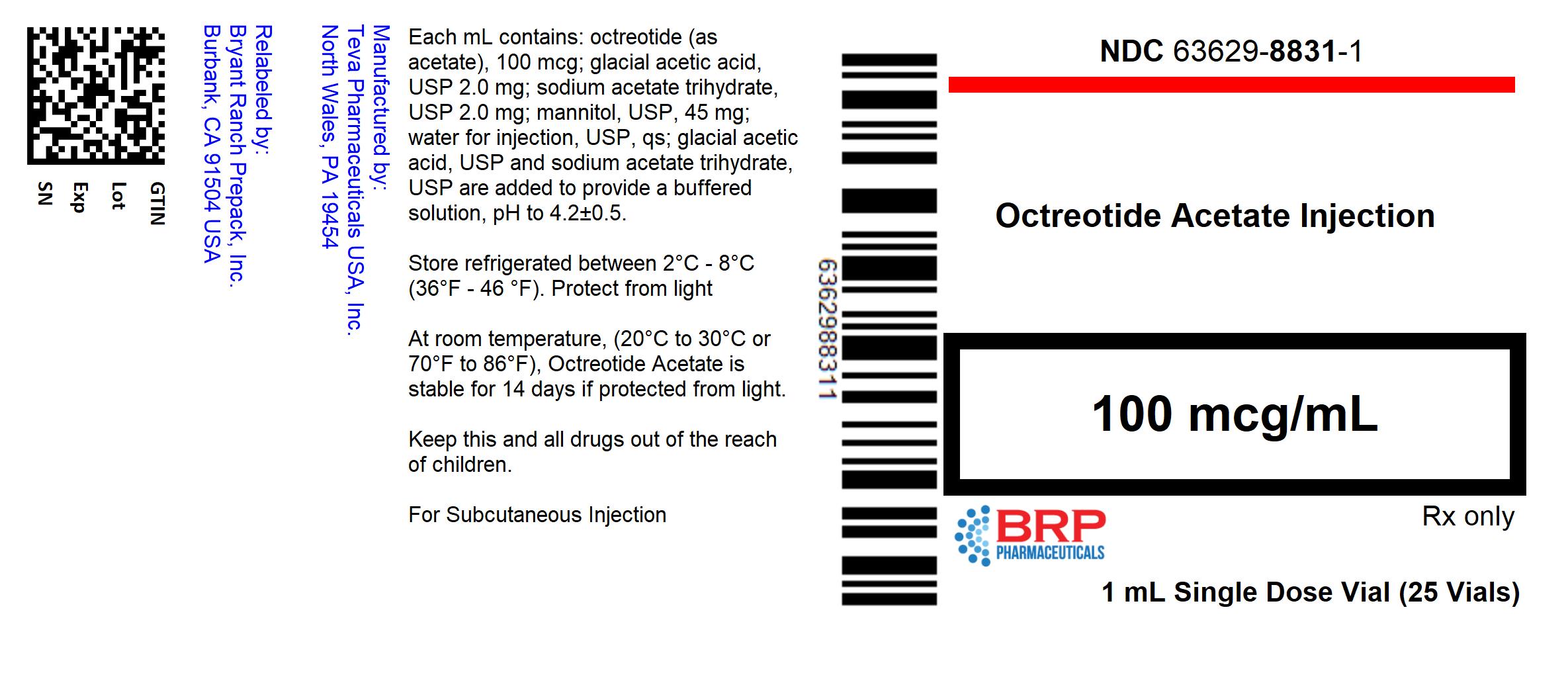 DRUG LABEL: Octreotide Acetate
NDC: 63629-8831 | Form: INJECTION, SOLUTION
Manufacturer: Bryant Ranch Prepack
Category: prescription | Type: HUMAN PRESCRIPTION DRUG LABEL
Date: 20220427

ACTIVE INGREDIENTS: OCTREOTIDE ACETATE 100 ug/1 mL
INACTIVE INGREDIENTS: ACETIC ACID; SODIUM ACETATE; MANNITOL; WATER

Octreotide Acetate Injection
Rx only

DESCRIPTION

Octreotide Acetate Injection, a cyclic octapeptide prepared as a clear sterile solution of octreotide, acetate salt, in a buffered acetate solution for administration by deep subcutaneous (intrafat) or intravenous injection. Octreotide acetate, known chemically as L-Cysteinamide, D-phenylalanyl-L-cysteinyl-L-phenylalanyl-D-tryptophyl-L-lysyl-L-threonyl-N-[2-hydroxy-1-(hydroxymethyl)propyl]-, cyclic (2→7)-disulfide; [R-(R*, R*)] acetate salt, is a long-acting octapeptide with pharmacologic actions mimicking those of the natural hormone somatostatin.

Octreotide Acetate Injection is available as: sterile 1 mL single-dose vials in 3 strengths, containing 50, 100, or 500 mcg octreotide (as acetate), and sterile 5 mL multiple dose vials in 2 strengths, containing 200 and 1000 mcg/mL of octreotide (as acetate).

Each single-dose vial also contains:
Glacial acetic acid, USP………….. | 2 mg
Sodium acetate trihydrate, USP…... | 2 mg
Mannitol, USP……………………. | 45 mg
Water for injection, USP…………. | qs to 1 mL
Each mL of the multiple dose vials also contains:
Glacial acetic acid, USP…………... | 2 mg
Sodium acetate trihydrate, USP…... | 2 mg
Phenol liquefied, USP……………... | 5 mg
Mannitol, USP……………………... | 45 mg
Water for injection, USP…………... | qs to 1 mL

Glacial acetic acid, USP and sodium acetate trihydrate, USP are added to provide a buffered solution, pH to 4.2 ± 0.5.

The molecular weight of octreotide acetate is 1019.3 (free peptide, C49H66N10O10S2) and its amino acid sequence is:

CLINICAL PHARMACOLOGY

Octreotide acetate exerts pharmacologic actions similar to the natural hormone, somatostatin. It is an even more potent inhibitor of growth hormone, glucagon, and insulin than somatostatin. Like somatostatin, it also suppresses LH response to GnRH, decreases splanchnic blood flow, and inhibits release of serotonin, gastrin, vasoactive intestinal peptide, secretin, motilin, and pancreatic polypeptide.

By virtue of these pharmacological actions, octreotide acetate has been used to treat the symptoms associated with metastatic carcinoid tumors (flushing and diarrhea), and Vasoactive Intestinal Peptide (VIP) secreting adenomas (watery diarrhea).

Octreotide acetate substantially reduces growth hormone and/or IGF-I (somatomedin C) levels in patients with acromegaly.

Single doses of octreotide acetate have been shown to inhibit gallbladder contractility and to decrease bile secretion in normal volunteers. In controlled clinical trials, the incidence of gallstone or biliary sludge formation was markedly increased (see WARNINGS).

Octreotide acetate suppresses secretion of thyroid stimulating hormone (TSH).

Pharmacokinetics

After subcutaneous injection, octreotide is absorbed rapidly and completely from the injection site. Peak concentrations of 5.2 ng/mL (100-mcg dose) were reached 0.4 hours after dosing. Using a specific radioimmunoassay, intravenous and subcutaneous doses were found to be bioequivalent. Peak concentrations and area under the curve (AUC) values were dose proportional after intravenous single doses up to 200 mcg and subcutaneous single doses up to 500 mcg and after subcutaneous multiple doses up to 500 mcg three times a day (1500 mcg/day).

In healthy volunteers, the distribution of octreotide from plasma was rapid (tα1/2 = 0.2 h), the volume of distribution (Vdss) was estimated to be 13.6 L, and the total body clearance ranged from 7 L/hr to 10 L/hr. In blood, the distribution into the erythrocytes was found to be negligible and about 65% was bound in the plasma in a concentration-independent manner. Binding was mainly to lipoprotein and, to a lesser extent, to albumin.

The elimination of octreotide from plasma had an apparent half-life of 1.7 to 1.9 hours compared with 1 to 3 minutes with the natural hormone. The duration of action of octreotide acetate is variable but extends up to 12 hours depending upon the type of tumor. About 32% of the dose is excreted unchanged into the urine. In an elderly population, dose adjustments may be necessary due to a significant increase in the half-life (46%) and a significant decrease in the clearance (26%) of the drug.

In patients with acromegaly, the pharmacokinetics differs somewhat from those in healthy volunteers. A mean peak concentration of 2.8 ng/mL (100 mcg dose) was reached in 0.7 hours after subcutaneous dosing. The volume of distribution (Vdss) was estimated to be 21.6 ± 8.5 L, and the total body clearance was increased to 18 L/h. The mean percent of the drug bound was 41.2%. The disposition and elimination half-lives were similar to normals.

In patients with renal impairment, the elimination of octreotide from plasma was prolonged and total body clearance reduced. In mild renal impairment (CLCR 40 to 60 mL/min), octreotide t1/2 was 2.4 hours and total body clearance was 8.8 L/hr, in moderate impairment (CLCR 10 to 39 mL/min) t1/2 was 3.0 hours and total body clearance 7.3 L/hr, and in severely renally impaired patients not requiring dialysis (CLCR < 10 mL/min) t1/2 was 3.1 hours and total body clearance was 7.6 L/hr. In patients with severe renal failure requiring dialysis, total body clearance was reduced to about half that found in healthy subjects (from approximately 10 L/hr to 4.5 L/hr).

Patients with liver cirrhosis showed prolonged elimination of drug, with octreotide t1/2 increasing to 3.7 hr and total body clearance decreasing to 5.9 L/hr, whereas patients with fatty liver disease showed t1/2 increased to 3.4 hr and total body clearance of 8.2 L/hr.

INDICATIONS AND USAGE

Acromegaly

Octreotide acetate injection is indicated to reduce blood levels of growth hormone and IGF-I (somatomedin C) in acromegaly patients who have had inadequate response to or cannot be treated with surgical resection, pituitary irradiation, and bromocriptine mesylate at maximally tolerated doses. The goal is to achieve normalization of growth hormone and IGF-I (somatomedin C) levels (see DOSAGE AND ADMINISTRATION). In patients with acromegaly, octreotide acetate injection reduces growth hormone to within normal ranges in 50% of patients and reduces IGF-I (somatomedin C) to within normal ranges in 50% to 60% of patients. Since the effects of pituitary irradiation may not become maximal for several years, adjunctive therapy with octreotide acetate injection to reduce blood levels of growth hormone and IGF-I (somatomedin C) offers potential benefit before the effects of irradiation are manifested.

Improvement in clinical signs and symptoms, or reduction in tumor size or rate of growth, was not shown in clinical trials performed with octreotide acetate injection; these trials were not optimally designed to detect such effects.

Carcinoid Tumors

Octreotide acetate injection is indicated for the symptomatic treatment of patients with metastatic carcinoid tumors where it suppresses or inhibits the severe diarrhea and flushing episodes associated with the disease.

Octreotide acetate injection studies were not designed to show an effect on the size, rate of growth or development of metastases.

Vasoactive Intestinal Peptide Tumors (VIPomas)

Octreotide acetate injection is indicated for the treatment of the profuse watery diarrhea associated with VIP-secreting tumors. Octreotide acetate injection studies were not designed to show an effect on the size, rate of growth or development of metastases.

CONTRAINDICATIONS

Sensitivity to this drug or any of its components.

WARNINGS

Single doses of octreotide acetate have been shown to inhibit gallbladder contractility and decrease bile secretion in normal volunteers. In clinical trials (primarily patients with acromegaly or psoriasis), the incidence of biliary tract abnormalities was 63% (27% gallstones, 24% sludge without stones, 12% biliary duct dilatation). The incidence of stones or sludge in patients who received octreotide acetate for 12 months or longer was 52%. Less than 2% of patients treated with octreotide acetate for 1 month or less developed gallstones. The incidence of gallstones did not appear related to age, sex or dose. Like patients without gallbladder abnormalities, the majority of patients developing gallbladder abnormalities on ultrasound had gastrointestinal symptoms. The symptoms were not specific for gallbladder disease. A few patients developed acute cholecystitis, ascending cholangitis, biliary obstruction, cholestatic hepatitis, or pancreatitis during octreotide acetate therapy or following its withdrawal. One patient developed ascending cholangitis during octreotide acetate therapy and died. There have been postmarketing reports of cholelithiasis (gallstones) resulting in complications requiring cholecystectomy.

If complications of cholelithiasis are suspected, discontinue octreotide acetate and treat appropriately.

PRECAUTIONS

General

Octreotide acetate alters the balance between the counter-regulatory hormones, insulin, glucagon and growth hormone, which may result in hypoglycemia or hyperglycemia. Octreotide acetate also suppresses secretion of thyroid stimulating hormone, which may result in hypothyroidism. Cardiac conduction abnormalities have also occurred during treatment with octreotide acetate. However, the incidence of these adverse events during long-term therapy was determined vigorously only in acromegaly patients who, due to their underlying disease and/or the subsequent treatment they receive, are at an increased risk for the development of diabetes mellitus, hypothyroidism, and cardiovascular disease. Although the degree to which these abnormalities are related to octreotide acetate therapy is not clear, new abnormalities of glycemic control, thyroid function and ECG developed during octreotide acetate therapy as described below.

Risk of Pregnancy with Normalization of IGF-1 and GH

Although acromegaly may lead to infertility, there are reports of pregnancy in acromegalic women. In women with active acromegaly who have been unable to become pregnant, normalization of GH and IGF-1 may restore fertility. Female patients of childbearing potential should be advised to use adequate contraception during treatment with octreotide.

The hypoglycemia or hyperglycemia which occurs during octreotide acetate therapy is usually mild, but may result in overt diabetes mellitus or necessitate dose changes in insulin or other hypoglycemic agents. Hypoglycemia and hyperglycemia occurred on octreotide acetate in 3% and 16% of acromegalic patients, respectively. Severe hyperglycemia, subsequent pneumonia, and death following initiation of octreotide acetate therapy was reported in one patient with no history of hyperglycemia.

In patients with concomitant Type I diabetes mellitus, octreotide acetate injection and octreotide acetate for injectable suspension are likely to affect glucose regulation, and insulin requirements may be reduced. Symptomatic hypoglycemia, which may be severe, has been reported in these patients. In non-diabetics and Type II diabetics with partially intact insulin reserves, octreotide acetate injection or octreotide acetate for injectable suspension administration may result in decreases in plasma insulin levels and hyperglycemia. It is therefore recommended that glucose tolerance and antidiabetic treatment be periodically monitored during therapy with these drugs.

In acromegalic patients, 12% developed biochemical hypothyroidism only, 8% developed goiter, and 4% required initiation of thyroid replacement therapy while receiving octreotide acetate. Baseline and periodic assessment of thyroid function (TSH, total and/or free T4) is recommended during chronic therapy.

In acromegalics, bradycardia (< 50 bpm) developed in 25%; conduction abnormalities occurred in 10% and arrhythmias occurred in 9% of patients during octreotide acetate therapy. Other EKG changes observed included QT prolongation, axis shifts, early repolarization, low voltage, R/S transition, and early R wave progression. These ECG changes are not uncommon in acromegalic patients. Dose adjustments in drugs such as beta-blockers that have bradycardia effects may be necessary. In one acromegalic patient with severe congestive heart failure, initiation of octreotide acetate therapy resulted in worsening of CHF with improvement when drug was discontinued. Confirmation of a drug effect was obtained with a positive rechallenge.

Several cases of pancreatitis have been reported in patients receiving octreotide acetate therapy.

Octreotide acetate may alter absorption of dietary fats in some patients.

In patients with severe renal failure requiring dialysis, the half-life of octreotide acetate may be increased, necessitating adjustment of the maintenance dosage.

Depressed vitamin B12 levels and abnormal Schilling's tests have been observed in some patients receiving octreotide acetate therapy, and monitoring of vitamin B12 levels is recommended during chronic octreotide acetate therapy.

Information for Patients

Careful instruction in sterile subcutaneous injection technique should be given to the patients and to other persons who may administer octreotide acetate injection. Inform patients that cholelithiasis has been reported with the use of octreotide acetate injection. Advise patients to contact their healthcare provider if they experience signs or symptoms of gallstones (cholelithiasis) or complications of gallstones (e.g., cholecystitis, cholangitis, and pancreatitis).

Laboratory Tests

Laboratory tests that may be helpful as biochemical markers in determining and following patient response depend on the specific tumor. Based on diagnosis, measurement of the following substances may be useful in monitoring the progress of therapy:

Acromegaly: | Growth Hormone, IGF-I (somatomedin C)
 | Responsiveness to octreotide acetate may be evaluated by determining growth hormone levels at 1 to 4 hour intervals for 8 to 12 hours post dose. Alternatively, a single measurement of IGF-I (somatomedin C) level may be made two weeks after drug initiation or dosage change.
Carcinoid: | 5-HIAA (urinary 5-hydroxyindole acetic acid), plasma serotonin, plasma Substance P
VIPoma: | VIP (plasma vasoactive intestinal peptide)

Baseline and periodic total and/or free T4 measurements should be performed during chronic therapy (see PRECAUTIONS, General).

Drug Interactions

Octreotide acetate has been associated with alterations in nutrient absorption, so it may have an effect on absorption of orally administered drugs. Concomitant administration of octreotide acetate with cyclosporine may decrease blood levels of cyclosporine and result in transplant rejection.

Patients receiving insulin, oral hypoglycemic agents, beta blockers, calcium channel blockers, or agents to control fluid and electrolyte balance, may require dose adjustments of these therapeutic agents.

Concomitant administration of octreotide and bromocriptine increases the availability of bromocriptine. Limited published data indicate that somatostatin analogs might decrease the metabolic clearance of compounds known to be metabolized by cytochrome P450 enzymes, which may be due to the suppression of growth hormones. Since it cannot be excluded that octreotide may have this effect, other drugs mainly metabolized by CYP3A4 and which have a low therapeutic index (e.g., quinidine, terfenadine) should therefore be used with caution.

Drug/Laboratory Test Interactions

No known interference exists with clinical laboratory tests, including amine or peptide determinations.

Carcinogenesis, Mutagenesis, Impairment of Fertility

Studies in laboratory animals have demonstrated no mutagenic potential of octreotide acetate.

No carcinogenic potential was demonstrated in mice treated subcutaneously for 85 to 99 weeks at doses up to 2000 mcg/kg/day (8 x the human exposure based on body surface area). In a 116-week subcutaneous study in rats, a 27% and 12% incidence of injection site sarcomas or squamous cell carcinomas was observed in males and females, respectively, at the highest dose level of 1250 mcg/kg/day (10 x the human exposure based on body surface area) compared to an incidence of 8% to 10% in the vehicle-control groups. The increased incidence of injection site tumors was most probably caused by irritation and the high sensitivity of the rat to repeated subcutaneous injections at the same site. Rotating injection sites would prevent chronic irritation in humans. There have been no reports of injection site tumors in patients treated with octreotide acetate for up to 5 years. There was also a 15% incidence of uterine adenocarcinomas in the 1250 mcg/kg/day females compared to 7% in the saline-control females and 0% in the vehicle-control females. The presence of endometritis coupled with the absence of corpora lutea, the reduction in mammary fibroadenomas, and the presence of uterine dilatation suggest that the uterine tumors were associated with estrogen dominance in the aged female rats which does not occur in humans.

Octreotide acetate did not impair fertility in rats at doses up to 1000 mcg/kg/day, which represents 7x the human exposure based on body surface area.

PREGNANCY

There are no adequate and well-controlled studies of octreotide use in pregnant women. Reproduction studies have been performed in rats and rabbits at doses up to 16 times the highest recommended human dose based on body surface area and revealed no evidence of harm to the fetus due to octreotide. However, because animal reproduction studies are not always predictive of human response, this drug should be used during pregnancy only if clearly needed.

In postmarketing data, a limited number of exposed pregnancies have been reported in patients with acromegaly. Most women were exposed to octreotide during the first trimester of pregnancy at doses ranging from 100 to 300 mcg/day of octreotide acetate injection s.c. or 20 to 30 mg/month of octreotide acetate for injectable suspension, however some women elected to continue octreotide therapy throughout pregnancy. In cases with a known outcome, no congenital malformations were reported.

Nursing Mothers

It is not known whether octreotide is excreted into human milk. Because many drugs are excreted in human milk, caution should be exercised when octreotide is administered to a nursing woman.

Pediatric Use

Safety and efficacy of octreotide acetate injection in the pediatric population have not been demonstrated.

No formal controlled clinical trials have been performed to evaluate the safety and effectiveness of octreotide acetate in pediatric patients under age 6 years. In postmarketing reports, serious adverse events, including hypoxia, necrotizing enterocolitis, and death, have been reported with octreotide acetate use in children, most notably in children under 2 years of age. The relationship of these events to octreotide has not been established as the majority of these pediatric patients had serious underlying co-morbid conditions.

The efficacy and safety of octreotide acetate using the octreotide acetate for injectable suspension formulation was examined in a single randomized, double-blind, placebo-controlled, six month pharmacokinetics study in 60 pediatric patient's age 6 to 17 years with hypothalamic obesity resulting from cranial insult. The mean octreotide concentration after 6 doses of 40 mg octreotide acetate for injectable suspension administered by IM injection every four weeks was approximately 3 ng/ml. Steady-state concentrations were achieved after 3 injections of a 40 mg dose. Mean BMI increased 0.1 kg/m^2 in octreotide acetate for injectable suspension-treated subjects compared to 0.0 kg/m^2 in saline control-treated subjects. Efficacy was not demonstrated. Diarrhea occurred in 11 of 30 (37%) patients treated with octreotide acetate for injectable suspension. No unexpected adverse events were observed. However, with octreotide acetate for injectable suspension 40 mg once a month, the incidence of new cholelithiasis in this pediatric population (33%) was higher than that seen in other adult indications such as acromegaly (22%) or malignant carcinoid syndrome (24%), where octreotide acetate for injectable suspension was 10 to 30 mg once a month.

Geriatric Use

Clinical studies of octreotide acetate injection did not include sufficient numbers of subjects aged 65 and over to determine whether they respond differently from younger subjects. Other reported clinical experience has not identified differences in responses between the elderly and younger patients. In general, dose selection for an elderly patient should be cautious, usually starting at the low end of the dosing range, reflecting the greater frequency of decreased hepatic, renal, or cardiac function, and of concomitant disease or other drug therapy.

ADVERSE REACTIONS

Gallbladder Abnormalities

Gallbladder abnormalities, especially stones and/or biliary sludge, frequently develop in patients on chronic octreotide acetate therapy (see WARNINGS).

Cardiac

In acromegalics, sinus bradycardia (< 50 bpm) developed in 25%; conduction abnormalities occurred in 10% and arrhythmias developed in 9% of patients during octreotide acetate therapy (see PRECAUTIONS, General).

Gastrointestinal

Diarrhea, loose stools, nausea and abdominal discomfort were each seen in 34% to 61% of acromegalic patients in U.S. studies although only 2.6% of the patients discontinued therapy due to these symptoms. These symptoms were seen in 5% to 10% of patients with other disorders.

The frequency of these symptoms was not dose-related, but diarrhea and abdominal discomfort generally resolved more quickly in patients treated with 300 mcg/day than in those treated with 750 mcg/day. Vomiting, flatulence, abnormal stools, abdominal distention, and constipation were each seen in less than 10% of patients.

In rare instances, gastrointestinal side effects may resemble acute intestinal obstruction, with progressive abdominal distension, severe epigastric pain, abdominal tenderness and guarding.

Hypo/Hyperglycemia

Hypoglycemia and hyperglycemia occurred in 3% and 16% of acromegalic patients, respectively, but only in about 1.5% of other patients. Symptoms of hypoglycemia were noted in approximately 2% of patients.

Hypothyroidism

In acromegalics, biochemical hypothyroidism alone occurred in 12% while goiter occurred in 6% during octreotide acetate therapy (see PRECAUTIONS, General). In patients without acromegaly, hypothyroidism has only been reported in several isolated patients and goiter has not been reported.

Other Adverse Events

Pain on injection was reported in 7.7%, headache in 6% and dizziness in 5%. Pancreatitis was also observed (see WARNINGS and PRECAUTIONS).

Other Adverse Events 1% to 4%

Other events (relationship to drug not established), each observed in 1% to 4% of patients, included fatigue, weakness, pruritus, joint pain, backache, urinary tract infection, cold symptoms, flu symptoms, injection site hematoma, bruise, edema, flushing, blurred vision, pollakiuria, fat malabsorption, hair loss, visual disturbance and depression.

Other Adverse Events < 1%

Events reported in less than 1% of patients and for which relationship to drug is not established are listed: Gastrointestinal: hepatitis, jaundice, increase in liver enzymes, GI bleeding, hemorrhoids, appendicitis, gastric/peptic ulcer, gallbladder polyp; Integumentary: rash, cellulitis, petechiae, urticaria, basal cell carcinoma; Musculoskeletal: arthritis, joint effusion, muscle pain, Raynaud's phenomenon; Cardiovascular: chest pain, shortness of breath, thrombophlebitis, ischemia, congestive heart failure, hypertension, hypertensive reaction, palpitations, orthostatic BP decrease, tachycardia; CNS: anxiety, libido decrease, syncope, tremor, seizure, vertigo, Bell's Palsy, paranoia, pituitary apoplexy, increased intraocular pressure, amnesia, hearing loss, neuritis; Respiratory: pneumonia, pulmonary nodule, status asthmaticus; Endocrine: galactorrhea, hypoadrenalism, diabetes insipidus, gynecomastia, amenorrhea, polymenorrhea, oligomenorrhea, vaginitis; Urogenital: nephrolithiasis, hematuria; Hematologic: anemia, iron deficiency, epistaxis; Miscellaneous: otitis, allergic reaction, increased CK, weight loss.

Evaluation of 20 patients treated for at least 6 months has failed to demonstrate titers of antibodies exceeding background levels. However, antibody titers to octreotide acetate were subsequently reported in three patients and resulted in prolonged duration of drug action in two patients. Anaphylactoid reactions, including anaphylactic shock, have been reported in several patients receiving octreotide acetate.

Postmarketing Experience

The following adverse reactions have been identified during the postapproval use of octreotide acetate. Because these reactions are reported voluntarily from a population of uncertain size, it is not always possible to reliably estimate their frequency or establish a causal relationship to drug exposure.

Hepatobiliary: cholelithiasis, cholecystitis, cholangitis and pancreatitis, which have sometimes required cholecystectomy

Gastrointestinal: intestinal obstruction

Hematologic: thrombocytopenia

To report SUSPECTED ADVERSE REACTIONS, contact Teva Pharmaceuticals USA, Inc. at 1-888-838-2872 or FDA at 1-800-FDA-1088 or www.fda.gov/medwatch.

OVERDOSAGE

A limited number of accidental overdoses of octreotide acetate in adults have been reported. In adults, the doses ranged from 2,400 to 6,000 mcg/day administered by continuous infusion (100 to 250 mcg/hour) or subcutaneously (1,500 mcg three times a day). Adverse events in some patients included arrhythmia, hypotension, cardiac arrest, brain hypoxia, pancreatitis, hepatitis steatosis, hepatomegaly, lactic acidosis, flushing, diarrhea, lethargy, weakness, and weight loss.

Octreotide acetate injection given in intravenous boluses of 1 mg (1000 mcg) to healthy volunteers did not result in serious ill effects, nor did doses of 30 mg (30,000 mcg) given intravenously over 20 minutes and of 120 mg (120,000 mcg) given intravenously over 8 hours to research patients.

If overdose occurs, symptomatic management is indicated. Up-to-date information about the treatment of overdose can often be obtained from the National Poison Control Center at 1-800-222-1222.

Drug Abuse and Dependence

There is no indication that octreotide acetate has potential for drug abuse or dependence. Octreotide acetate levels in the central nervous system are negligible, even after doses up to 30,000 mcg.

DOSAGE AND ADMINISTRATION

Octreotide acetate injection may be administered subcutaneously or intravenously. Subcutaneous injection is the usual route of administration of octreotide acetate injection for control of symptoms. Pain with subcutaneous administration may be reduced by using the smallest volume that will deliver the desired dose. Multiple subcutaneous injections at the same site within short periods of time should be avoided. Sites should be rotated in a systematic manner.

Parenteral drug products should be inspected visually for particulate matter and discoloration prior to administration. Do not use if particulates and/or discoloration are observed. Proper sterile technique should be used in the preparation of parenteral admixtures to minimize the possibility of microbial contamination. Octreotide acetate injection is not compatible in Total Parenteral Nutrition (TPN) solutions because of the formation of a glycosyl octreotide conjugate which may decrease the efficacy of the product.

Octreotide acetate injection is stable in sterile isotonic saline solutions or sterile solutions of dextrose 5% in water for 24 hours. It may be diluted in volumes of 50 to 200 mL and infused intravenously over 15 to 30 minutes or administered by IV push over 3 minutes. In emergency situations (e.g., carcinoid crisis), it may be given by rapid bolus.

The initial dosage is usually 50 mcg administered twice or three times daily. Upward dose titration is frequently required. Dosage information for patients with specific tumors follows.

Acromegaly

Dosage may be initiated at 50 mcg three times a day. Beginning with this low dose may permit adaptation to adverse gastrointestinal effects for patients who will require higher doses. IGF-I (somatomedin C) levels every 2 weeks can be used to guide titration. Alternatively, multiple growth hormone levels at 0 to 8 hours after octreotide acetate injection administration permit more rapid titration of dose. The goal is to achieve growth hormone levels less than 5 ng/mL or IGF-I (somatomedin C) levels less than 1.9 unit/mL in males and less than 2.2 unit/mL in females. The dose most commonly found to be effective is 100 mcg three times a day, but some patients require up to 500 mcg three times a day for maximum effectiveness. Doses greater than 300 mcg/day seldom result in additional biochemical benefit, and if an increase in dose fails to provide additional benefit, the dose should be reduced. IGF-I (somatomedin C) or growth hormone levels should be reevaluated at 6 month intervals.

Octreotide acetate injection should be withdrawn yearly for approximately 4 weeks from patients who have received irradiation to assess disease activity. If growth hormone or IGF-I (somatomedin C) levels increase and signs and symptoms recur, octreotide acetate injection therapy may be resumed.

Carcinoid Tumors

The suggested daily dosage of octreotide acetate injection during the first 2 weeks of therapy ranges from 100 to 600 mcg/day in 2 to 4 divided doses (mean daily dosage is 300 mcg). In the clinical studies, the median daily maintenance dosage was approximately 450 mcg, but clinical and biochemical benefits were obtained in some patients with as little as 50 mcg, while others required doses up to 1500 mcg/day. However, experience with doses above 750 mcg/day is limited.

VIPomas

Daily dosages of 200 to 300 mcg in 2 to 4 divided doses are recommended during the initial 2 weeks of therapy (range: 150 to 750 mcg) to control symptoms of the disease. On an individual basis, dosage may be adjusted to achieve a therapeutic response, but usually doses above 450 mcg/day are not required.

HOW SUPPLIED

Octreotide Acetate Injection is available in 1 mL single-dose vials as follows:

NDC Number | Octreotide Acetate Injection | Vial/Package Size
63629-8831-1 | 100 mcg/mL | 1 mL single-dose vial 25 per shelf tray

Storage
For prolonged storage, Octreotide Acetate Injection single-dose vials and multiple dose vials should be stored at refrigerated temperatures 2°C to 8°C (36°F to 46°F) and protected from light. At room temperature (20°C to 30°C or 70°F to 86°F), Octreotide Acetate is stable for 14 days if protected from light. The solution can be allowed to come to room temperature prior to administration. Do not warm artificially. After initial use, multiple-dose vials should be discarded within 14 days. Single-dose vials should be opened just prior to administration and the unused portion discarded. Dispose unused product or waste properly.

Teva Pharmaceuticals USA, Inc.
North Wales, PA 19454

Rev. F 5/2019

PACKAGE LABEL

Octreotide Acetate Injection #25